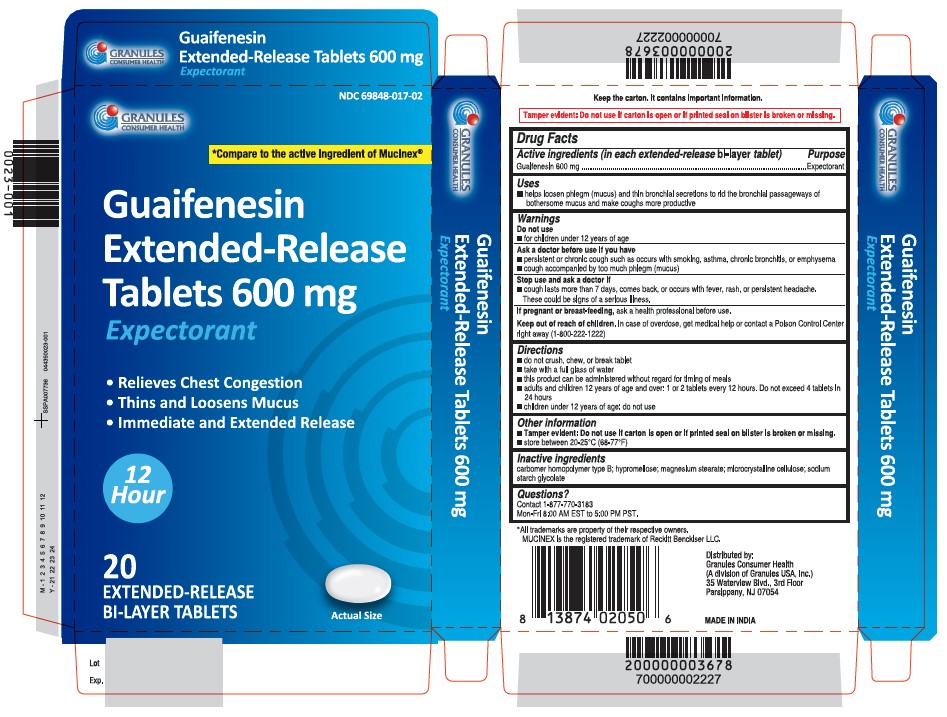 DRUG LABEL: Guaifenesin
NDC: 69848-017 | Form: TABLET, EXTENDED RELEASE
Manufacturer: GRANULES USA, INC.
Category: otc | Type: HUMAN OTC DRUG LABEL
Date: 20251222

ACTIVE INGREDIENTS: GUAIFENESIN 600 mg/1 1
INACTIVE INGREDIENTS: CARBOMER HOMOPOLYMER TYPE B (ALLYL SUCROSE CROSSLINKED); HYPROMELLOSE 2910 (5 MPA.S); SODIUM STARCH GLYCOLATE TYPE A; MICROCRYSTALLINE CELLULOSE; MAGNESIUM STEARATE

Guaifenesin
Extended-Release Tablets 600 mg
Expectorant
12 HR

Active ingredients (in each extended-release bi-layer tablet)

Guaifenesin 600 mg

Purpose

Expectorant

Uses

■ helps loosen phlegm (mucus) and thin bronchial secretions to rid the bronchial passageways of bothersome mucus and make coughs more productive

Do not use

■ for children under 12 years of age

Ask a doctor before use if you have

■ persistent or chronic cough such as occurs with smoking, asthma, chronic bronchitis, or emphysema
■ cough accompanied by too much phlegm (mucus)

Stop use and ask doctor if

■ cough lasts more than 7 days, comes back, or occurs with fever, rash, or persistent headache. These could be signs of a serious illness.

If pregnant or breat-feeding,

ask a health professional before use.

Keep out of reach of children

In case of overdose, get medical help or contact a Poison Control Center right away (1-800-222-1222)

Directions

■ do not crush, chew, or break tablet
■ take with a full glass of water
■ this product can be administered without regard for timing of meals
■ adults and children 12 years of age and over: 1 or 2 tablets every 12 hours. Do not exceed 4 tablets in 24 hours
■ children under 12 years of age: do not use

Other information

■ Tamper evident: Do not use if carton is open or if printed seal on blister is broken or missing.
■ store between 20-25°C (68-77°F)

Inactive ingredients

carbomer homopolymer type B; hypromellos, magnesium stearate, microcrystalline cellulose, sodium starch glycolate

Questions?

Contact 1-877-770-3183
Mon-Fri 8:00 AM EST to 5:00 PM PST.